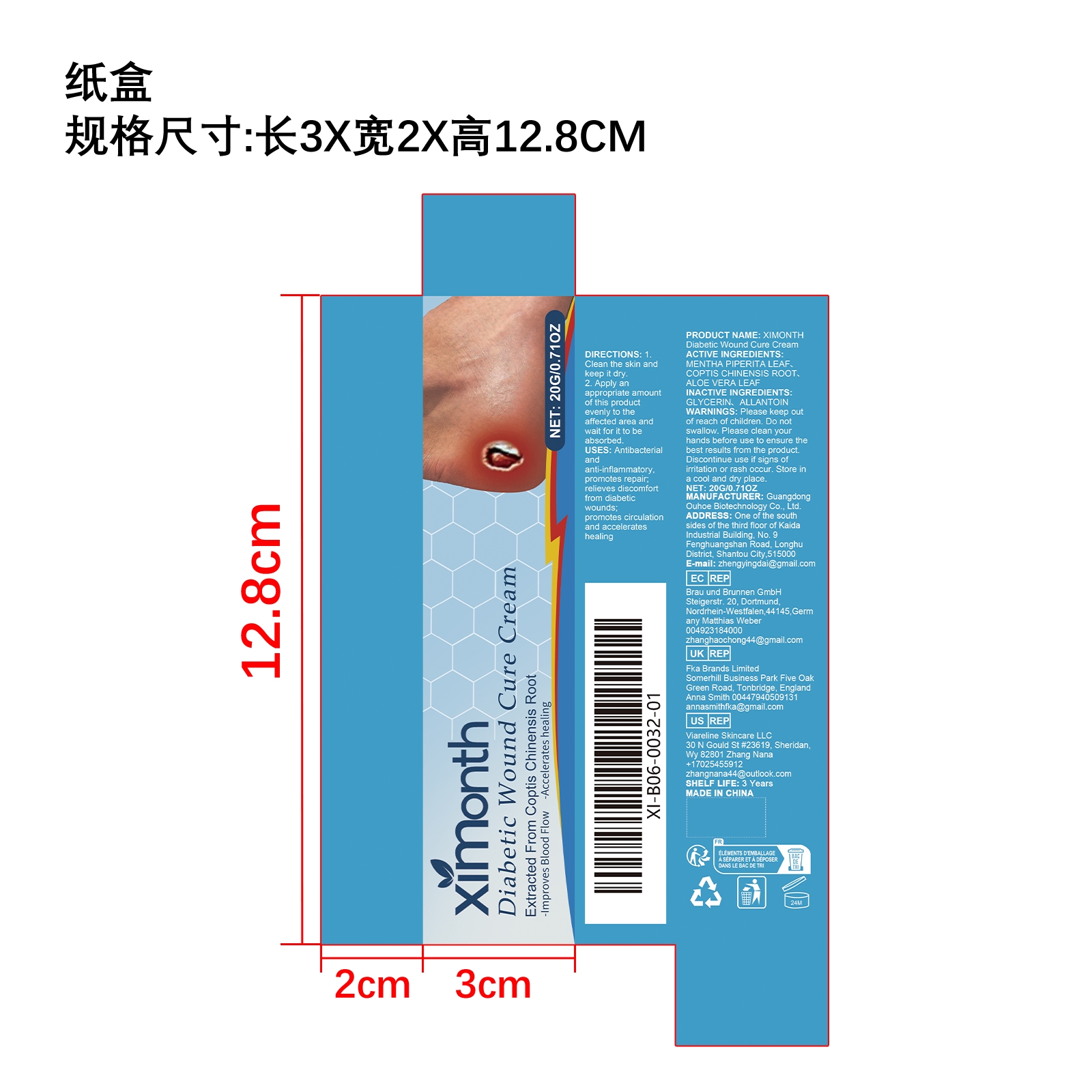 DRUG LABEL: XIMONTH Diabetic Wound Cure Cream
NDC: 84744-055 | Form: CREAM
Manufacturer: Guangdong Ouhoe Biotechnology Co., Ltd.
Category: otc | Type: HUMAN OTC DRUG LABEL
Date: 20241022

ACTIVE INGREDIENTS: ALOE VERA LEAF 5 g/20 g; MENTHA PIPERITA LEAF 2 g/20 g; COPTIS CHINENSIS ROOT 5 g/20 g
INACTIVE INGREDIENTS: GLYCERIN 4 g/20 g; ALLANTOIN 4 g/20 g

Active Ingredient(s)

MENTHA PIPERITA LEAF、COPTIS CHINENSIS ROOT、ALOE VERA LEAF

Purpose

Antibacterial andanti-inflammatory, promotes repair; relieves discomfort from diabeticwounds;promotes circulation and accelerates healing

Use

1. Clean the skin and keep it dry.
2. Apply an appropriate amount of this product evenly to the affected area and wait for it to be absorbed.

Warnings

Please keep out of reach of children.Do not swallow.Please clean your hands before use to ensure the best results from the product.Discontinue use if signs of irritation or rash occur.Store in a cool and dry place.

Do not use

Discontinue use if signs of irritation or rash occur.

Stop Use

Discontinue use if signs of irritation or rash occur.

KEEP OUT OF REACH OF CHILDREN

Please keep out of reach of children. Do not swallow.

STORAGE AND HANDLING

Store in a cool and dry place.

INACTIVE INGREDIENT

GLYCERIN、ALLANTOIN